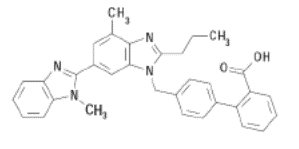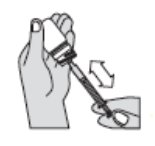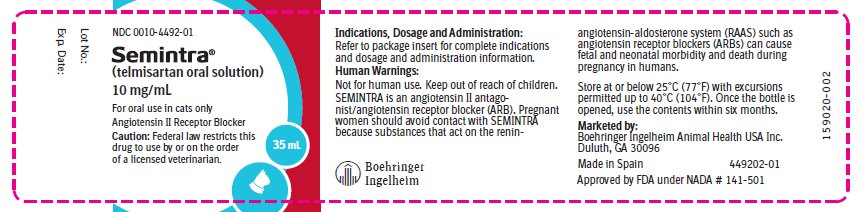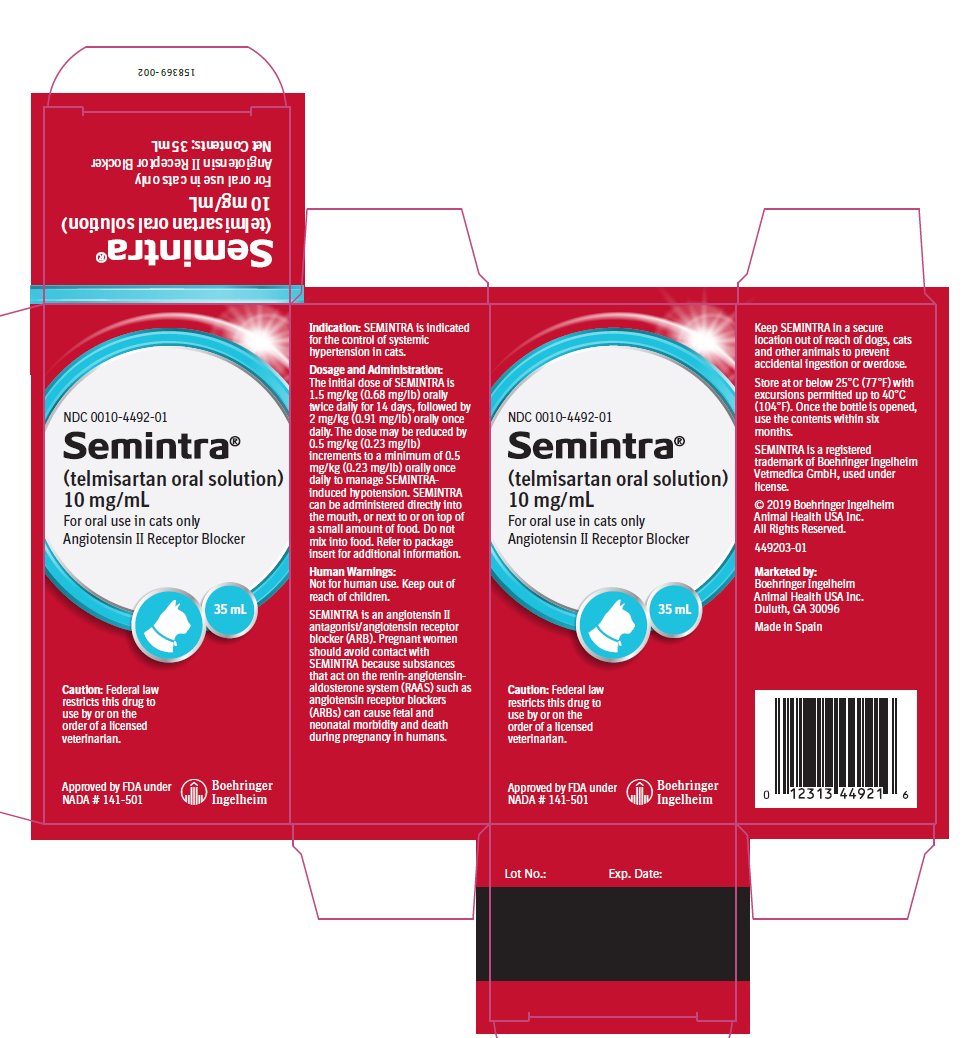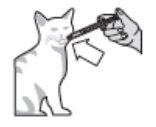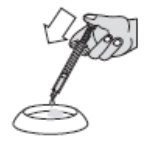 DRUG LABEL: Semintra
NDC: 0010-4492 | Form: SOLUTION
Manufacturer: Boehringer Ingelheim Animal Health USA Inc.
Category: animal | Type: PRESCRIPTION ANIMAL DRUG LABEL
Date: 20210825

ACTIVE INGREDIENTS: TELMISARTAN 10 mg/1 mL

Semintra® (telmisartan oral solution)
10 mg/mL

For oral use in cats only
Angiotensin II Receptor Blocker

Caution:

Federal law restricts this drug to use by or on the order of a licensed veterinarian.

Description:

SEMINTRA (telmisartan oral solution) is a clear, colorless to yellowish viscous solution containing 10 mg/mL telmisartan. Telmisartan is an orally active, non-peptide, selective angiotensin II subtype 1 (AT1) receptor blocker. The chemical name of telmisartan is 4'-[(1,4’-dimethyl-2'propyl[2,6'-bi-1H-benzimidazol]-1'-yl)methyl]-[1,1'-biphenyl]-2-carboxylic acid. Its empirical formula is C33H30N4O2, its molecular weight is 514.63, and its structural formula is:

Indication:

SEMINTRA is indicated for the control of systemic hypertension in cats.

Dosage and Administration:

Always provide the Client Information Sheet with each prescription.

The initial dose of SEMINTRA is 1.5 mg/kg (0.68 mg/lb) orally twice daily for 14 days, followed by 2 mg/kg (0.91 mg/lb) orally once daily. The dose may be reduced by 0.5 mg/kg (0.23 mg/lb) increments to a minimum of 0.5 mg/kg (0.23 mg/lb) orally once daily to manage SEMINTRA-induced hypotension. SEMINTRA can be administered directly into the mouth, or next to or on top of a small amount of food. Do not mix into food.

SEMINTRA should be administered using the dosing syringe provided in the package. The dosing syringe fits onto the bottle and has 0.1 mL incremental marks. The dose should be rounded to the nearest 0.1 mL. After administration close the bottle tightly with the cap. Rinse the dosing syringe with water and let air dry.

If the cat vomits within 30 minutes of dosing, the cat may be re-dosed.

Information for Cat Owners

Always provide the Client Information Sheet with each prescription and review it with the cat owner. Advise cat owners that adverse reactions can occur with use of SEMINTRA. The most common adverse reactions reported during the field studies included vomiting, diarrhea, lethargy, weight loss, anemia and dehydration.

Contraindications:

Do not use in cats with a hypersensitivity to telmisartan.

Human Warnings:

Not for human use. Keep out of reach of children.

SEMINTRA is an angiotensin II antagonist/angiotensin receptor blocker (ARB). Pregnant women should avoid contact with SEMINTRA because substances that act on the renin-angiotensin-aldosterone system (RAAS) such as angiotensin receptor blockers (ARBs) can cause fetal and neonatal morbidity and death during pregnancy in humans.

Precautions:

SEMINTRA has not been evaluated in cats with systolic blood pressure >200 mm Hg.

SEMINTRA can cause mild anemia or non-regenerative anemia. Cats should be monitored for anemia when initiating treatment with SEMINTRA.

SEMINTRA may cause inappetence and weight loss in some cats. Cats should be monitored for weight loss when initiating treatment with SEMINTRA. Use with caution in cats with a history of vomiting, inappetence or weight loss.

The safe use of SEMINTRA in cats with hepatic disease has not been evaluated. SEMINTRA is metabolized by the liver.

The safe use of SEMINTRA has not been evaluated in cats less than 9 months of age.

The safe use of SEMINTRA has not been evaluated in cats that are pregnant, lactating, or intended for breeding. See Human Warnings.

The safe use with other anti-hypertensive medications has not been evaluated.

Adverse Reactions:

28-day Field Effectiveness Study
Safety was evaluated in a 28-day field study in 288 cats (192 SEMINTRA group cats, 96 control group cats) that received at least one dose of study drug. The control product was a vehicle control without telmisartan. Cats enrolled in the study had a median age of 14 years (7-20 years), and weighed 1.93-11.4 kg. SEMINTRA was administered orally at 1.5 mg/kg twice daily for 14 days, then 2 mg/kg once daily until study end; the control was administered at a volume equivalent to SEMINTRA. One hundred fourteen (59.4%) SEMINTRA group cats and 42 (43.8%) control group cats had at least one adverse reaction. Adverse reactions that occurred in at least 5% of either treatment group are presented in Table 1 below.

Table 1 Adverse Reactions in the 28-Day Field Study

Clinical Sign | SEMINTRA; N=192 | Control; N=96
Vomiting | 46 (24.0%) | 14 (14.6%)
Diarrhea | 18 (9.4%) | 4 (4.2%)
Lethargy | 13 (6.8%) | 3 (3.1%)
Weight loss | 13 (6.8%) | 5 (5.2%)
Decreased appetite/inappetence | 13 (6.8%) | 7 (7.3%)
Non-regenerative anemia | 11 (5.7%) | 2 (2.1%)
Dehydration | 10 (5.2%) | 4 (4.2%)
Retinal lesions (target organ damage) | 4 (2.1%) | 6 (6.3%)

Additional adverse reactions that occurred in <5% of the SEMINTRA group included (in order of decreasing frequency): anorexia, gagging, arrhythmia, cough, heart murmur, and regenerative anemia. Additional adverse reactions representing 2-5% of the control group included azotemia, not drinking and renal failure.

Seven cats (five SEMINTRA and two control) either died or were euthanized during the study. None of the SEMINTRA group deaths were considered related to treatment.

5-month Field Effectiveness and Safety Study
The long-term safety of SEMINTRA was evaluated in an open label, 5 month field effectiveness and safety study in 107 cats that received at least one dose of SEMINTRA. Cats enrolled in the study had a mean age of 14.1 years (7-20 years) and weighed 1.92-11.4 kg. SEMINTRA was administered orally at 2 mg/kg once daily. Ninety-four cats (87.9%) had at least one adverse reaction during the study. Adverse reactions that occurred in at least 5% of cats are presented in Table 2 below.

Table 2 Adverse Reactions in the 5-Month Study

Clinical Sign | SEMINTRA N=107
Weight loss | 37 (34.6%)
Vomiting | 32 (29.9%)
Dehydration | 18 (16.8%)
Non-regenerative anemia | 17 (15.8%)
Anorexia | 14 (13.1%)
Diarrhea | 12 (11.2%)
Lethargy | 12 (11.2%)
Decreased appetite/inappetence | 11 (10.3%)
Heart murmur | 10 (9.3%)
Death, Euthanasia, Found dead | 9 (8.4%)
Cough | 8 (7.5%)
Retinal lesions (target organ damage) | 6 (5.6%)

Adverse reactions representing <5% of the study population were (in order of decreasing frequency): elevated liver enzymes, renal failure, tachycardia, arrhythmia, azotemia, depression, loose stool, constipation, gagging, hypotension, regenerative anemia, renal insufficiency, and vocalization.

Nine cats died or were euthanized during the study. Three cats had progressive chronic kidney disease that may have been affected by telmisartan treatment, concurrent disease, or inadequate control of hypertension. The other six cats died of causes unrelated to treatment (e.g. neoplasia).

To report suspected adverse drug events, for technical assistance, or to obtain a copy of the Safety Data Sheet (SDS), contact Boehringer Ingelheim Animal Health USA Inc. at 1-888-637-4251. For additional information about adverse drug experience reporting for animal drugs, contact FDA at 1-888-FDA-VETS or online at www.fda.gov/reportanimalae.

Clinical Pharmacology:

Telmisartan is a selective angiotensin II subtype AT1 receptor blocker, with no relevant affinity for other receptors in general receptor-binding assays. Telmisartan is metabolized to the 1-O-acylglucuronide of telmisartan, which, in cats treated for 6 days at 1 mg/kg, was shown to be present in the plasma at levels approximately 21% of that of unchanged parent compound.

Following an oral dose of 1 mg/kg telmisartan once daily for five days, the time to reach mean peak plasma concentration (Tmax) was 21 minutes and 32 minutes for fasted and fed cats, respectively. There was a higher systemic exposure to telmisartan in the fasted cats based on the maximum concentration (Cmax) and area under the concentration vs time curve (AUC). The mean terminal elimination half-life was approximately 8 hours. The mean systemic exposure of telmisartan (Cmax and AUC) was approximately 60% lower for female cats compared to male cats. However, dose adjustment for female cats is not necessary. An increase in dose from 1 to 5 mg/kg once daily resulted in a greater than proportional increase in telmisartan exposure. There could be low to moderate accumulation of drug upon repeated once daily or twice daily administrations of 1.5-2 mg/kg.

Effectiveness:

Effectiveness was demonstrated in a 28-day multi-center, controlled, randomized and masked field study in client-owned cats with hypertension, and in an open-label 5-month field study.

28-Day Field Study
In the 28-day study, 288 cats with hypertension (systolic blood pressure [SBP] 160-200 mmHg) were enrolled in the study and randomized to treatment with SEMINTRA (telmisartan oral solution) (n=192) or vehicle control (n=96). The study population included cats with hypertension associated with chronic kidney disease or controlled hyperthyroidism, or idiopathic hypertension. The per protocol population for effectiveness was 141 SEMINTRA treated cats and 79 control cats. SEMINTRA was administered orally at 1.5 mg/kg twice daily for 14 days, then 2 mg/kg once daily until study end; the vehicle control was administered at a mL/kg volume equivalent to SEMINTRA. The two primary variables for effectiveness were comparison of the SEMINTRA and control group mean SBP (mSBP) from baseline to Day 14, and a decrease in mSBP >20 mmHg in the SEMINTRA group from baseline to Day 28. Cats with SBP >180 mmHg at Days 14 or 28 were rescued and removed from the study. There was a statistically significant difference between the mSBP for the SEMINTRA group compared to the control group at Day 14 (p=0.0005). At Day 14 the SEMINTRA group mSBP decreased by 23.2 mmHg, and the control group mSBP decreased by 7.3 mmHg. At Day 28, the SEMINTRA group mSBP decreased 23.9 mmHg compared to baseline.

5-Month Field Study
One hundred-seven cats from the SEMINTRA group that had successfully completed the 28-day study were enrolled in a 5-month open label study. At the beginning of the 5-month study most cats were administered SEMINTRA at 2 mg/kg once daily. Cats that experienced hypotension (defined as SBP <120 mmHg) at 2 mg/kg once daily could have the SEMINTRA dose reduced to 1 mg/kg once daily. Cats that experienced hypotension at 1 mg/kg once daily could have the SEMINTRA dose reduced again to 0.5 mg/kg once daily. Cats were evaluated for SBP, target organ damage (TOD; primarily assessed by retinal photographs), clinical pathology and adverse reactions. SBP was measured on Days 28, 56, 98, 140 and 182 and retinal photographs and clinical pathology were collected on Days 28, 98 and 182. Seventy-three (68.2%) cats completed the study (Day 182), 8 cats were removed for hypertension (SBP >180 mmHg), 2 cats were removed for hypotension, 10 cats were removed by the owner or for owner non-compliance, 8 cats were removed for new or worsening TOD, and 6 cats were removed for adverse reactions unrelated to TOD. Twenty-six cats had dose reductions to 1 mg/kg once daily to manage hypotension. Of these 26 cats, 10 had an additional dose reduction to 0.5 mg/kg once daily.

Table 3 Distribution of Cats by SBP Range and Study Day in the 5-Month Study a

SBP Range (mm Hg) | Baseline; N=107; n (%) | Day 28; N=107; n (%) | Day 56; N=102; n (%) | Day 98; N=91; n (%) | Day 140; N=80; n (%) | Day 182; N=69; n (%)
< 150 | 0; (0%) | 58; (54.2%) | 55; (53.9%) | 61; (67%) | 44; (55%) | 41; (59.4%)
> 150–160 | 4; (3.7%) | 19; (17.8%) | 19; (18.6%) | 17; (18.7%) | 21; (26.2%) | 16; (23.2%)
> 160–170 | 38; (35.5%) | 18; (16.8%) | 14; (13.7%) | 10; (11%) | 12; (15%) | 7; (10.1%)
> 170–180 | 28; (26.2%) | 12; (11.2%) | 10; (9.8%) | 2; (2.2%) | 3; (3.8%) | 4; (5.8%)
> 180 | 37; (34.6%) | 0; (0%) | 4; (3.9%) | 1; (1.1%) | 0; (0%) | 1; (1.5%)

a SBP obtained at unscheduled visits are not represented. Cats that were removed for missing >3 doses prior to SBP measurement are not included.

The most commonly used concomitant treatments during the 5-month study included (in order of frequency) antibiotics, anesthesia/sedatives/analgesia, nutritional supplements, vaccines, prescription diets, antiparasitics, thyroid treatment, antiemetics and fluid therapy.

Animal Safety:

In a six-month target animal safety study, healthy cats 9 to 13 months old were administered telmisartan orally, once daily at 0, 1, 3, or 5 mg/kg body weight.

Control cats (0 mg/kg) received saline at a volume equal to the 5 mg/kg dose. There were eight cats per group (4 males, 4 females).

All cats survived the study, and there were no telmisartan-related effects on clinical observations, physical examination, body weight, ophthalmic examination, coagulation parameters, urinalysis, and gross necropsy.

Blood pressure was lower in the groups administered telmisartan compared to the control group. Blood pressure was lower starting at week 4 in the 1 mg/kg group, at week 2 in the 3 mg/kg group, and during the first week in the 5 mg/kg group. This is an expected pharmacologic effect of telmisartan. Food consumption in the 3 and 5 mg/kg group cats was lower than that of the control group.

Telmisartan-related effects on hematology parameters included lower red blood cell count, hemoglobin, hematocrit, and reticulocytes in the 3 and 5 mg/kg group cats. One 5 mg/kg group cat also had mild generalized depletion of the hematopoietic cells on bone marrow histology. In some 5 mg/kg group cats, decreases in red blood cell precursors on bone marrow cytology were considered telmisartan-related.

Blood urea nitrogen (BUN) was statistically significantly higher for the 3 mg/kg group at weeks 12 and 16, and for the 5 mg/kg group at weeks 2, 4, 7, 12, 16, 20, and 25, when compared to the control group. There were no clinical signs associated with the changes in BUN.

There was a telmisartan-related effect on lower heart weight in the 3 and 5 mg/kg groups compared to the control group, but the histopathology was normal in all treated cats. On kidney histology, there was minimal to mild hypertrophy of the juxtaglomerular apparatus in the 1, 3, and 5 mg/kg group cats. Kidney histology was normal in control group cats.

Storage Conditions:

Store at or below 25°C (77°F) with excursions permitted up to 40°C (104°F). Once the bottle is opened, use the contents within six months.

How Supplied:

SEMINTRA (telmisartan oral solution), 10 mg/mL, 35 mL fill volume, is supplied in a 45 mL plastic bottle with a dosing syringe. NDC 0010-4492-01

Approved by FDA under NADA # 141-501

Marketed by:
Boehringer Ingelheim Animal Health USA Inc.

Duluth, GA 30096

Made in Spain

SEMINTRA is a registered trademark of Boehringer Ingelheim Vetmedica GmbH, used under license.

© 2019 Boehringer Ingelheim Animal Health USA Inc. All Rights Reserved.

Revised 11/2019

449201-01

Client Information Sheet

The Client Information Sheet contains important information about SEMINTRA. You should read this information before you start giving SEMINTRA and review it each time the prescription is refilled as there may be new information. This sheet is provided only as a summary and does not take the place of instructions from your veterinarian. Talk with your veterinarian if you do not understand any of this information or if you want to know more about SEMINTRA.

What is SEMINTRA?
SEMINTRA (telmisartan oral solution) is used to control high blood pressure in cats.

What should I tell my veterinarian about my cat before starting SEMINTRA?

- Tell your veterinarian about other medications your pet is taking, including prescription drugs, over the counter drugs, heartworm preventatives, flea & tick medications, and vitamins and supplements, including herbal medications.
- Tell your veterinarian if your cat is pregnant, nursing, or you intend to breed him/her.
- Tell your veterinarian if your cat has any other serious health conditions, anemia (low red blood cell count), vomiting or diarrhea, decreased appetite or weight loss.

Talk to your veterinarian about:

- How often your veterinarian should recheck your cat’s blood pressure while taking SEMINTRA
- The risks and benefits of taking SEMINTRA

What are some of the possible side effects of SEMINTRA?
Like all drugs, SEMINTRA may cause side effects, even at the prescribed dose. Serious side effects can occur, with or without warning, and in some situations result in death. Contact your veterinarian immediately if your cat develops a medical problem or side effect while taking SEMINTRA.

The most common side effects which can occur with SEMINTRA include vomiting, diarrhea, lethargy, weight loss, anemia (low red blood cell count) and dehydration.

There are other side effects which may occur. For a complete list, ask your veterinarian.

To report a suspected adverse reaction (side effects) contact Boehringer Ingelheim Animal Health USA Inc. at 1-888-637-4251.

How do I give SEMINTRA to my cat?
SEMINTRA should be given to your cat in their mouth (orally) or next to or on top of a small amount of food. Do not mix into food.

Follow your veterinarian’s instructions for how much and how often to give SEMINTRA.

Give SEMINTRA using the dosing syringe provided in the package. The dosing syringe fits into the bottle opening and has 0.1 mL marks to use for measuring the dose.

Remove the cap from the bottle and gently push the end of the dosing syringe into the bottle opening.

Turn the bottle/syringe upside down.

Pull the plunger out and fill the dosing syringe to the dose prescribed by your veterinarian.

Turn the bottle upright and remove the dosing syringe from the bottle.

Put the end of the dosing syringe into your cat’s mouth, and push the plunger to give the dose…

Or put the dose next to or on top a small amount of food. Do not mix into food. If SEMINTRA is put onto food, make sure your cat eats the food and the entire dose.

If your cat vomits within the 30 minutes of giving the SEMINTRA (telmisartan oral solution) dose, your cat can be given the same dose again. If your cat vomits more than 30 minutes after giving SEMINTRA, do not give SEMINTRA again until the next scheduled dose.

After dosing, replace the cap on the bottle and close tightly. Rinse the SEMINTRA dosing syringe with water and let air dry.

What should I do if my cat gets more than the prescribed amount of SEMINTRA?
Your cat may develop low blood pressure or other side effects. Contact your veterinarian immediately.

Human Warnings:
SEMINTRA is not for use in humans.

You should keep SEMINTRA in a secure storage area out of the reach of children.

Pregnant women should avoid contact with SEMINTRA, because other similar drugs have been found to harm the unborn baby during pregnancy.

If SEMINTRA is accidentally ingested, contact a physician. It is important to show the treating physician a copy of the package insert, label, or client information sheet. SEMINTRA is an angiotensin II receptor blocker.

This client information sheet contains a summary of important information about SEMINTRA. For more detailed information about SEMINTRA, talk with your veterinarian.

Storage Statement: SEMINTRA (telmisartan oral solution) can be stored at 77°F and can be transported for short periods up to 104°F. Once the bottle is opened, use the contents within six months.

Revised 11/2019

Principal Display Panel - 35 mL Container Label

NDC 0010-4492-01

Semintra®
(telmisartan oral solution)
10 mg/mL

For oral use in cats only
Angiotensin II Receptor Blocker

Caution: Federal law restricts this drug to use by or on the order of a licensed veterinarian.

35 mL

Principal Display Panel - 35 mL Display Carton

NDC 0010-4492-01

Semintra®
(telmisartan oral solution)
10 mg/mL

For oral use in cats only
Angiotensin II Receptor Blocker

Caution: Federal law restricts this drug to use by or on the order of a licensed veterinarian.

Approved by FDA under NADA # 141-501